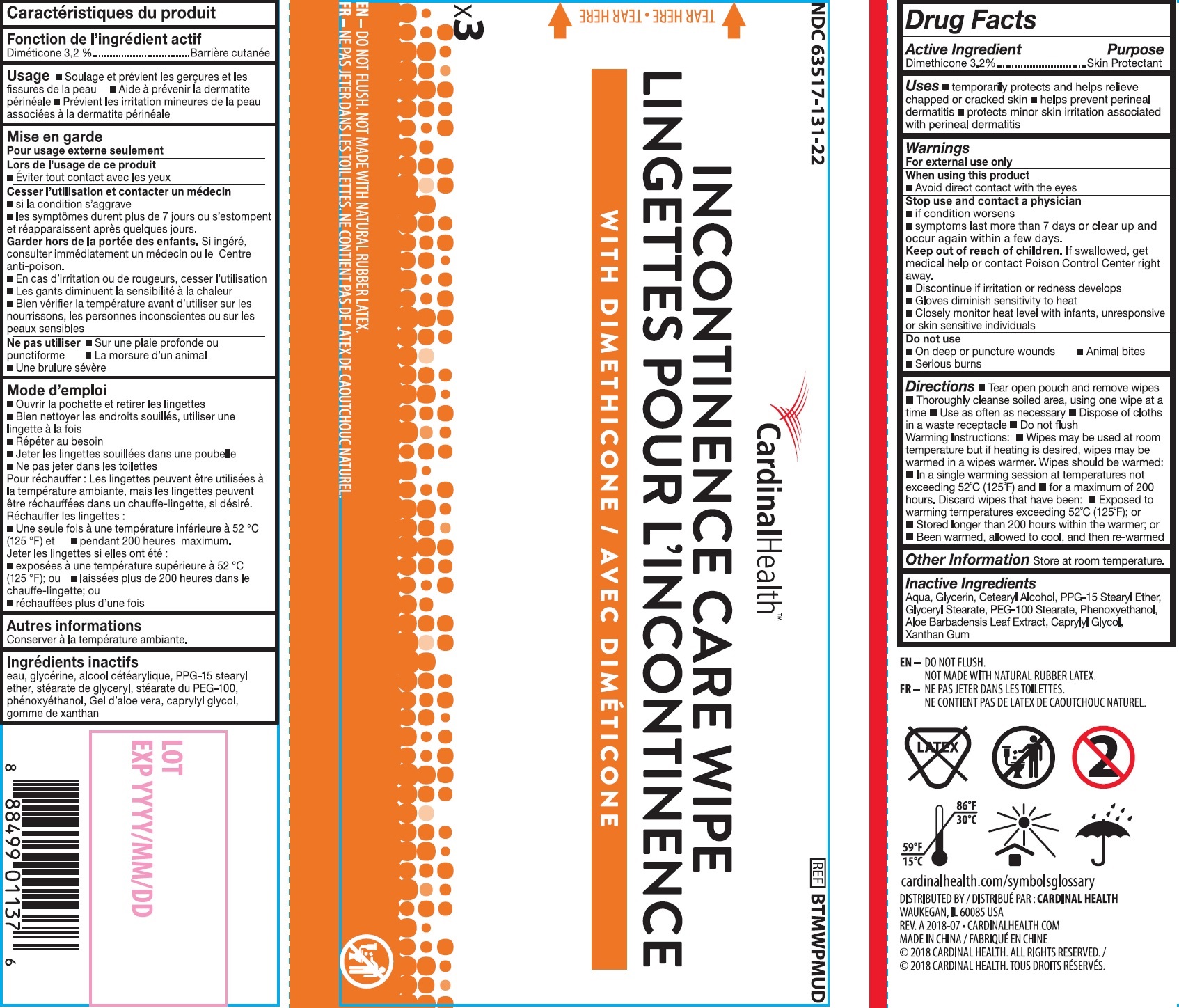 DRUG LABEL: INCONTINENCE CARE WIPE
NDC: 63517-131 | Form: SWAB
Manufacturer: Cardinal Health 200, Inc.
Category: otc | Type: HUMAN OTC DRUG LABEL
Date: 20260115

ACTIVE INGREDIENTS: DIMETHICONE 32 mg/1 g
INACTIVE INGREDIENTS: WATER; GLYCERIN; CETOSTEARYL ALCOHOL; PPG-15 STEARYL ETHER; GLYCERYL MONOSTEARATE; PEG-100 STEARATE; PHENOXYETHANOL; ALOE VERA LEAF; CAPRYLYL GLYCOL; XANTHAN GUM

INCONTINENCE CARE WIPE

Active Ingredient

Dimethicone 3.2%

Purpose

Skin Protectant

Uses

- temporarily protects and helps relieve chapped or cracked skin
- helps prevent perineal dermatitis
- protects minor skin irritation associated with perineal dermatitis

Warnings

For external use only

When using this product

- Avoid direct contact with the eyes

Stop use and contact a physician

- if condition worsens
- symptoms last more than 7 days or clear up and occur again within a few days.

Keep out of reach of children.

If swallowed, get medical help or contact Posion Control Center right away.

- Discontinue if irritation or redness develops
- Gloves diminish sensitivity to heat
- Closely monitor heat level with infants, unresponsive or skin sensitive individuals

Do not use

- On deep or puncture wounds
- Animal bites
- Serious burns

Directions

- Tear open pouch and remove wipes
- Thoroughly cleanse soiled area, using one wipe at a time
- Use as often as necessary
- Dispose of cloths in a waste receptacle
- Do not flush

- Wipes may be used at room temperature but if heating is desired, wipes may be warmed in a wipes warmer. Wipes should be warmed:
- In a single warming session at temperatures not exceeding 52°C (125°F) and
- for a maximum of 200 hours. Discard wipes that have been:
- Exposed to warming temperatures exceeding 52°C (125°F); or
- Stored longer than 200 hours within the warmer; or
- Been warmed, allowed to cool, and then re-warmed

Warming Instructions:

Other Information

Store at room temperature.

Inactive Ingredients

Aqua, Glycerin, Cetearyl Alcohol, PPG-15 Stearyl Ether, Glyceryl Stearate, PEG-100 Stearate, Phenoxyethanol, Aloe Barbadensis Leaf Extract, Caprylyl Glycol, Xanthan Gum